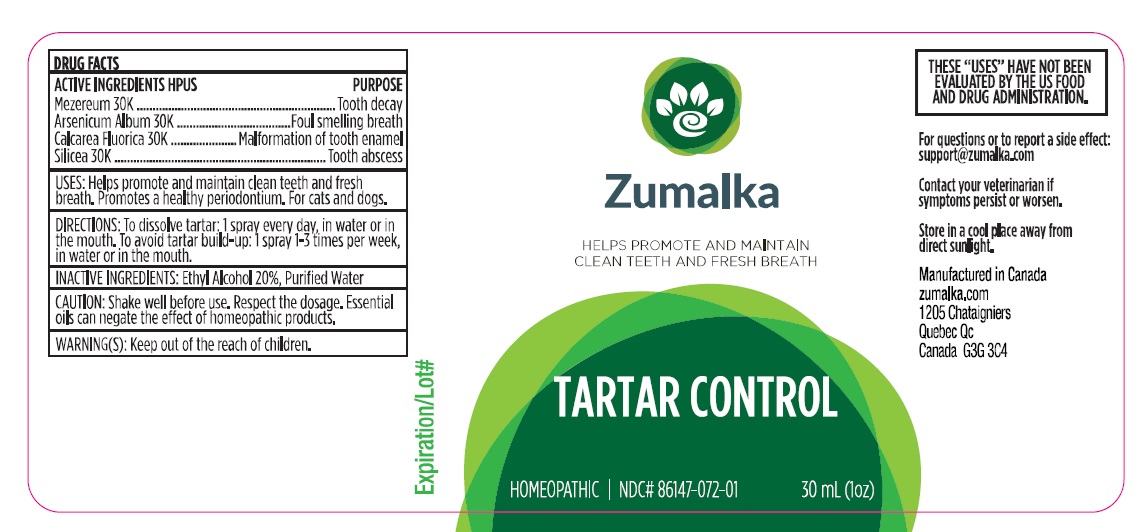 DRUG LABEL: TARTAR CONTROL
NDC: 86147-072 | Form: LIQUID
Manufacturer: Groupe Cyrenne Inc.
Category: homeopathic | Type: OTC ANIMAL DRUG LABEL
Date: 20251120

ACTIVE INGREDIENTS: DAPHNE MEZEREUM BARK 30 [kp_C]/30 mL; ARSENIC TRIOXIDE 30 [kp_C]/30 mL; SILICON DIOXIDE 30 [kp_C]/30 mL; CALCIUM FLUORIDE 30 [kp_C]/30 mL
INACTIVE INGREDIENTS: ALCOHOL; WATER

Active ingredients

Mezereum 30k, Arsenicum Album 30k, Calcarea Fluorica 30k, Silicea 30k

Uses

Helps promote and maintain clean teeth and a fresh breath. Promotes a healthy periodontium. For cats and dogs only.

Warnings

Shake well before use. Respect the dosage. Essential oils can negate the effects of homeopathic products. Store in a cool place away from direct sunlight. Keep out of reach of children.

Direction

To dissolve tartar: 1 spray every day, in water or in the mouth. To avoid tartar build-up: 1 spray 1-3 per week in water or in the mouth.

Inactive ingredients

Ethyl alcohol 20%, purified water

Other information

The letters "HPUS" indicate that the active ingredients are in the official Homeopathic Pharmacopoeia of the United States. Homeopathic remedy. Store at room temperature.